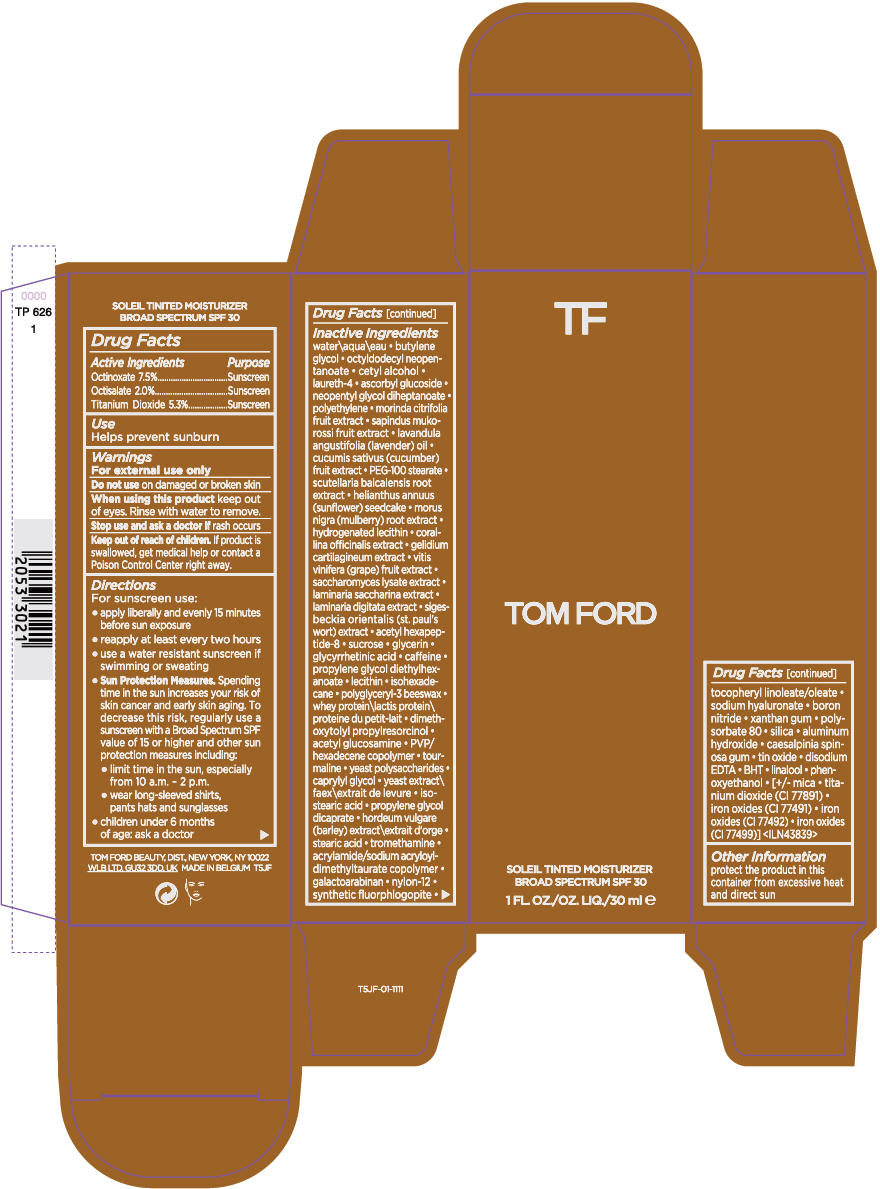 DRUG LABEL: TOM FORD SOLEIL TINTED MOISTURIZER  BROAD SPECTRUM SPF 30
NDC: 76398-005 | Form: CREAM
Manufacturer: TOM FORD BEAUTY DIST
Category: otc | Type: HUMAN OTC DRUG LABEL
Date: 20171011

ACTIVE INGREDIENTS: OCTINOXATE 0.0825 g/1 mL; OCTISALATE 0.022 g/1 mL; TITANIUM DIOXIDE 0.0583 g/1 mL
INACTIVE INGREDIENTS: WATER; BUTYLENE GLYCOL; OCTYLDODECYL NEOPENTANOATE; CETYL ALCOHOL; LAURETH-4; ASCORBYL GLUCOSIDE; NEOPENTYL GLYCOL DIHEPTANOATE; HIGH DENSITY POLYETHYLENE; NONI FRUIT; SAPINDUS MUKOROSSI FRUIT; LAVENDER OIL; CUCUMBER; PEG-100 STEARATE; SCUTELLARIA BAICALENSIS ROOT; HELIANTHUS ANNUUS SEEDCAKE; MORUS NIGRA ROOT; HYDROGENATED SOYBEAN LECITHIN; CORALLINA OFFICINALIS; GELIDIUM CARTILAGINEUM; WINE GRAPE; SACCHAROMYCES LYSATE; SACCHARINA LATISSIMA; LAMINARIA DIGITATA; ACETYL HEXAPEPTIDE-8; SUCROSE; GLYCERIN; ENOXOLONE; CAFFEINE; PROPYLENE GLYCOL DIETHYLHEXANOATE; ISOHEXADECANE; DIMETHOXYTOLYL PROPYLRESORCINOL; N-ACETYLGLUCOSAMINE; CAPRYLYL GLYCOL; ISOSTEARIC ACID; PROPYLENE GLYCOL DICAPRATE; STEARIC ACID; TROMETHAMINE; GALACTOARABINAN; NYLON-12; HYALURONATE SODIUM; BORON NITRIDE; XANTHAN GUM; POLYSORBATE 80; SILICON DIOXIDE; ALUMINUM HYDROXIDE; CAESALPINIA SPINOSA RESIN; STANNIC OXIDE; EDETATE DISODIUM ANHYDROUS; BUTYLATED HYDROXYTOLUENE; LINALOOL, (+/-)-; PHENOXYETHANOL; MICA; FERRIC OXIDE RED; FERRIC OXIDE YELLOW; FERROSOFERRIC OXIDE

TOM FORD SOLEIL TINTED MOISTURIZER BROAD SPECTRUM SPF 30

Drug Facts

ACTIVE INGREDIENT

Active Ingredients | Purpose
Octinoxate 7.5% | Sunscreen
Octisalate 2.0% | Sunscreen
Titanium Dioxide 5.3% | Sunscreen

Use

Helps prevent sunburn

Warnings

For external use only

Do not use on damaged or broken skin

When using this product keep out of eyes. Rinse with water to remove.

Stop use and ask a doctor if rash occurs

Keep out of reach of children. If product is swallowed, get medical help or contact a Poison Control Center right away.

Directions

For sunscreen use:

- apply liberally and evenly 15 minutes before sun exposure
- reapply at least every two hours
- use a water resistant sunscreen if swimming or sweating
- Sun Protection Measures. Spending time in the sun increases your risk of skin cancer and early skin aging. To decrease this risk, regularly use a sunscreen with a Broad Spectrum SPF value of 15 or higher and other sun protection measures including:
  - limit time in the sun, especially from 10 a.m. - 2 p.m.
  - wear long-sleeved shirts, pants hats and sunglasses
- children under 6 months of age: ask a doctor

Inactive Ingredients

water\aqua\eau • butylene glycol • octyldodecyl neopentanoate • cetyl alcohol • laureth-4 • ascorbyl glucoside • neopentyl glycol diheptanoate • polyethylene • morinda citrifolia fruit extract • sapindus mukorossi fruit extract • lavandula angustifolia (lavender) oil • cucumis sativus (cucumber) fruit extract • PEG-100 stearate • scutellaria baicalensis root extract • helianthus annuus (sunflower) seedcake • morus nigra (mulberry) root extract • hydrogenated lecithin • corallina officinalis extract • gelidium cartilagineum extract • vitis vinifera (grape) fruit extract • saccharomyces lysate extract • laminaria saccharina extract • laminaria digitata extract • sigesbeckia orientalis (st. paul's wort) extract • acetyl hexapeptide-8 • sucrose • glycerin • glycyrrhetinic acid • caffeine • propylene glycol diethylhexanoate • lecithin • isohexadecane • polyglyceryl-3 beeswax • whey protein\lactis protein\proteine du petit-lait • dimethoxytolyl propylresorcinol • acetyl glucosamine • PVP/hexadecene copolymer • tourmaline • yeast polysaccharides • caprylyl glycol • yeast extract\faex\extrait de levure • isostearic acid • propylene glycol dicaprate • hordeum vulgare (barley) extract\extrait d'orge • stearic acid • tromethamine • acrylamide/sodium acryloyldimethyltaurate copolymer • galactoarabinan • nylon-12 • synthetic fluorphlogopite • tocopheryl linoleate/oleate • sodium hyaluronate • boron nitride • xanthan gum • polysorbate 80 • silica • aluminum hydroxide • caesalpinia spinosa gum • tin oxide • disodium EDTA • BHT • linalool • phenoxyethanol • [+/- mica • titanium dioxide (CI 77891) • iron oxides (CI 77491) • iron oxides (CI 77492) • iron oxides (CI 77499)] <ILN43839>

Other Information

protect the product in this container from excessive heat and direct sun

PRINCIPAL DISPLAY PANEL - 30 ml Bottle Carton

TF

TOM FORD

SOLEIL TINTED MOISTURIZER
BROAD SPECTRUM SPF 30

1 FL OZ./OZ. LIQ./30 ml e